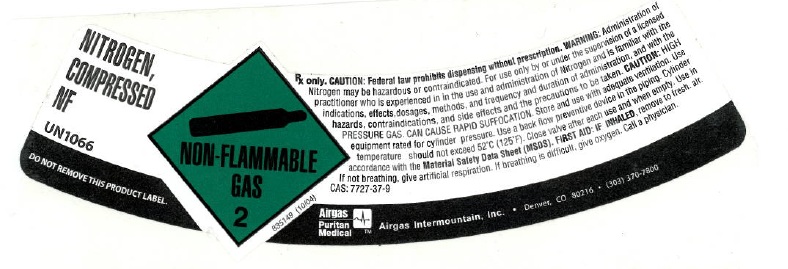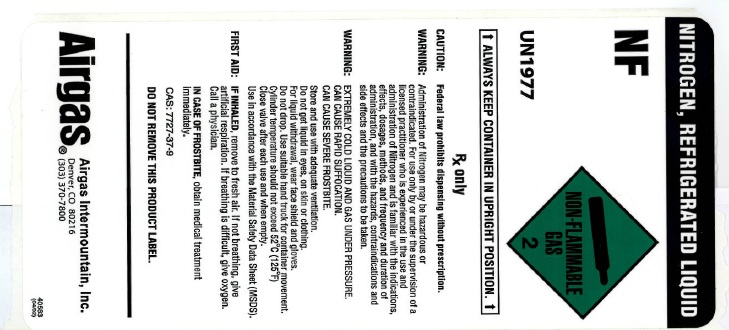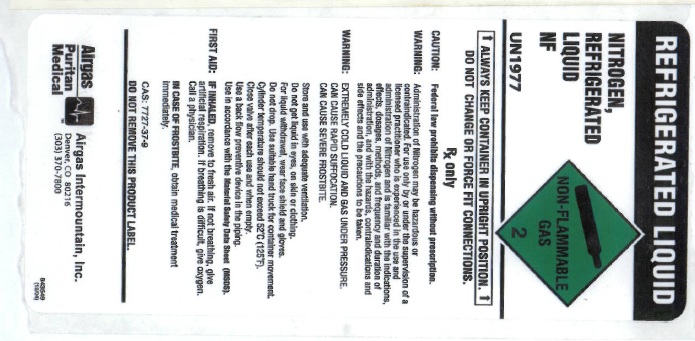 DRUG LABEL: Nitrogen
NDC: 58420-002 | Form: GAS
Manufacturer: Airgas Intermountain Inc
Category: prescription | Type: HUMAN PRESCRIPTION DRUG LABEL
Date: 20100623

ACTIVE INGREDIENTS: Nitrogen 992 mL/1 L

nitrogen

PACKAGE LABEL

NITROGEN, COMPRESSED NF UN1066
DO NOT REMOVE THIS PRODUCT LABEL. NON-FLAMMABLE GAS 2 835149 (10/04)
Rx only. CAUTION: Federal law prohibits dispensing without prescription. WARNING: Administration of Nitrogen may be hazardous or contraindicated. For use only by or under supervision of a licensed practitioner who is experienced in the use and administration of Nitrogen and is familiar with the indications, effects, dosages, methods, and frequency and duration of administration, and with the hazards, contraindications, and side effects and the precautions to be taken. CAUTION: HIGH PRESSURE GAS. CAN CAUSE RAPID SUFFOCATION. Store and use with adequate ventilation. Use equipment rated for cylinder pressure. Use a back flow preventive device in the piping. Cylinder temperatures should not exceed 52C (125F). Close valve after each use and when empty. Use in accordance with the Material Safety Data Sheet (MSDS). FIRST AID: IF INHALED, remove to fresh air. If not breathing, give artificial respiration. If breathing is difficult, give oxygen. Call a physician. CAS: 7727-37-9
AIRGAS PURITAN MEDICAL Airgas Intermountain, Inc. Denver, CO 80216 (303) 370-7800

PACKAGE LABEL

NITROGEN, REFRIGERATED LIQUID NF UN1977
NON-FLAMMABLE GAS 2 ALWAYS KEEP CONTAINER IN UPRIGHT POSITION
Rx only. CAUTION: Federal law prohibits dispensing without prescription. WARNING: Administration of Nitrogen may be hazardous or contraindicated. For use only by or under supervision of a licensed practitioner who is experienced in the use and administration of Nitrogen and is familiar with the indications, effects, dosages, methods, and frequency and duration of administration, and with the hazards, contraindications, and side effects and the precautions to be taken. WARNING: EXTREMELY COLD LIQUID AND GAS UNDER PRESSURE. CAN CAUSE RAPID SUFFOCATION. CAN CAUSE SEVERE FROSTBITE. Store and use with adequate ventilation. Do not get liquid in eyes, on skin, or clothing. For liquid withdrawal, use face shield and gloves. Do not drop. Use suitable hand truck for container movement. Cylinder temperatures should not exceed 52C (125F). Close valve after each use and when empty. Use in accordance with the Material Safety Data Sheet (MSDS). FIRST AID: IF INHALED, remove to fresh air. If not breathing, give oxygen. If breathing is difficult, give oxygen. Call a physician. IN CASE OF FROSTBITE, obtain medical treatment immediately. CAS: 7727-37-9 DO NOT REMOVE THIS PRODUCT LABEL.
AIRGAS Airgas Intermountain, Inc. Denver, CO 80216 (303) 370-7800
40583 (04/02)

PACKAGE LABEL

REFRIGERATED LIQUID
NITROGEN, REFRIGERATED LIQUID NF UN1977
NON-FLAMMABLE GAS 2 ALWAYS KEEP CONTAINER IN UPRIGHT POSITION DO NOT CHANGE OR FORCE FIT CONNECTIONS.
Rx only. CAUTION: Federal law prohibits dispensing without prescription. WARNING: Administration of Nitrogen may be hazardous or contraindicated. For use only by or under supervision of a licensed practitioner who is experienced in the use and administration of Nitrogen and is familiar with the indications, effects, dosages, methods, and frequency and duration of administration, and with the hazards, contraindications, and side effects and the precautions to be taken. WARNING: EXTREMELY COLD LIQUID AND GAS UNDER PRESSURE. CAN CAUSE RAPID SUFFOCATION. CAN CAUSE SEVERE FROSTBITE. Store and use with adequate ventilation. Do not get liquid in eyes, on skin, or clothing. For liquid withdrawal, use face shield and gloves. Do not drop. Use suitable hand truck for container movement. Cylinder temperatures should not exceed 52C (125F). Close valve after each use and when empty. Use a backflow preventive device in the piping. Use in accordance with the Material Safety Data Sheet (MSDS). FIRST AID: IF INHALED, remove to fresh air. If not breathing, give oxygen. If breathing is difficult, give oxygen. Call a physician. IN CASE OF FROSTBITE, obtain medical treatment immediately. CAS: 7727-37-9 DO NOT REMOVE THIS PRODUCT LABEL.
AIRGAS PURITAN MEDICAL Airgas Intermountain, Inc. Denver, CO 80216 (303) 370-7800
B43649 (12/04)